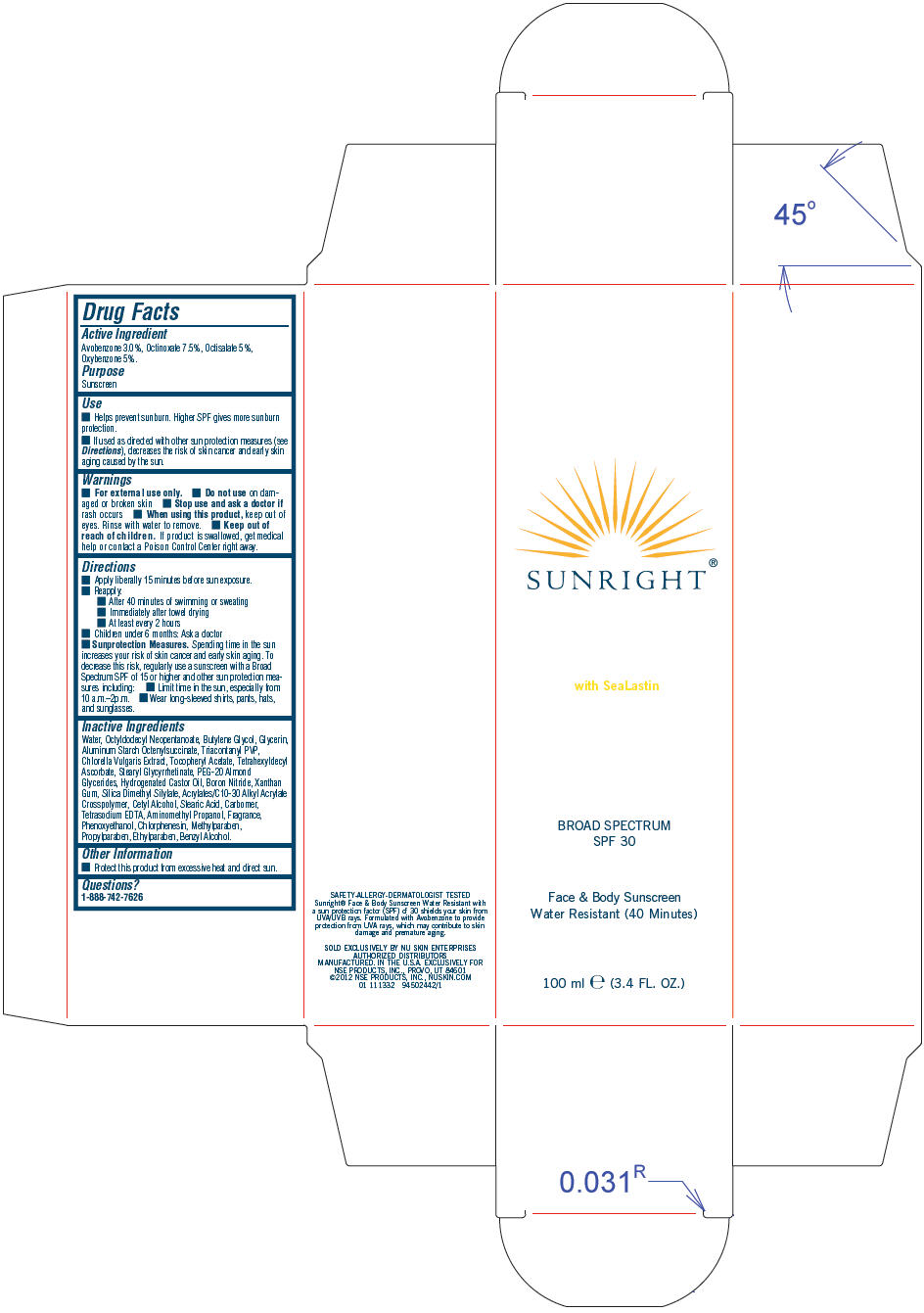 DRUG LABEL: Sunright Broad Spectrum SPF 30
NDC: 62839-1332 | Form: LOTION
Manufacturer: NSE Products, Inc.
Category: otc | Type: HUMAN OTC DRUG LABEL
Date: 20130520

ACTIVE INGREDIENTS: Avobenzone 30 mg/1 mL; Octinoxate 75 mg/1 mL; Octisalate 50 mg/1 mL; Oxybenzone 50 mg/1 mL
INACTIVE INGREDIENTS: Water; Octyldodecyl Neopentanoate; Butylene Glycol; Glycerin; Aluminum Starch Octenylsuccinate; Chlorella Vulgaris; Tetrahexyldecyl Ascorbate; Hydrogenated Castor Oil; Boron Nitride; Xanthan Gum; Cetyl Alcohol; Stearic Acid; Edetate Sodium; Aminomethylpropanol; Propylparaben; Phenoxyethanol; Chlorphenesin; Methylparaben; Ethylparaben; Benzyl Alcohol

Sunright® Broad Spectrum SPF 30

Drug Facts

Active Ingredient

Avobenzone 3.0%, Octinoxate 7.5%, Octisalate 5%, Oxybenzone 5%.

Purpose

Sunscreen

Use

- Helps prevent sunburn. Higher SPF gives more sunburn protection.
- If used as directed with other sun protection measures (see Directions), decreases the risk of skin cancer and early skin aging caused by the sun.

Warnings

- For external use only.

- Do not use on damaged or broken skin

- Stop use and ask a doctor if rash occurs

- When using this product, keep out of eyes. Rinse with water to remove.

- Keep out of reach of children. If product is swallowed, get medical help or contact a Poison Control Center right away.

Directions

- Apply liberally 15 minutes before sun exposure.
- Reapply:
  - After 40 minutes of swimming or sweating
  - Immediately after towel drying
  - At least every 2 hours
- Children under 6 months: Ask a doctor
- Sunprotection Measures. Spending time in the sun increases your risk of skin cancer and early skin aging. To decrease this risk, regularly use a sunscreen with a Broad Spectrum SPF of 15 or higher and other sun protection measures including:
  - Limit time in the sun, especially from 10 a.m.–2p.m.
  - Wear long-sleeved shirts, pants, hats, and sunglasses.

Inactive Ingredients

Water, Octyldodecyl Neopentanoate, Butylene Glycol, Glycerin, Aluminum Starch Octenylsuccinate, Triacontanyl PVP, Chlorella Vulgaris Extract, Tocopheryl Acetate, Tetrahexyldecyl Ascorbate, Stearyl Glycyrrhetinate, PEG-20 Almond Glycerides, Hydrogenated Castor Oil, Boron Nitride, Xanthan Gum, Silica Dimethyl Silylate, Acrylates/C10-30 Alkyl Acrylate Crosspolymer, Cetyl Alcohol, Stearic Acid, Carbomer, Tetrasodium EDTA, Aminomethyl Propanol, Fragrance, Phenoxyethanol, Chlorphenesin, Methylparaben, Propylparaben, Ethylparaben, Benzyl Alcohol.

Other Information

- Protect this product from excessive heat and direct sun.

Questions?

1-888-742-7626

PRINCIPAL DISPLAY PANEL - 100 ml Tube Carton

SUNRIGHT®

with SeaLastin

BROAD SPECTRUM
SPF 30

Face & Body Sunscreen
Water Resistant (40 Minutes)

100 ml e (3.4 FL. OZ.)